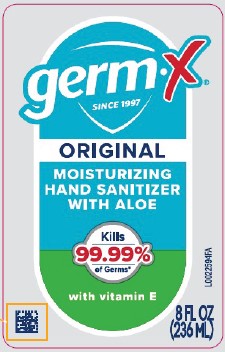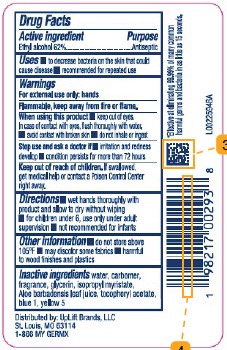 DRUG LABEL: Hand Sanitizer with Aloe
NDC: 83986-826 | Form: GEL
Manufacturer: UpLift Brands, LLC
Category: otc | Type: HUMAN OTC DRUG LABEL
Date: 20260217

ACTIVE INGREDIENTS: ALCOHOL 62 mL/100 mL
INACTIVE INGREDIENTS: WATER; CARBOMER HOMOPOLYMER, UNSPECIFIED TYPE; GLYCERIN; ISOPROPYL MYRISTATE; ALOE VERA LEAF; .ALPHA.-TOCOPHEROL ACETATE; FD&C BLUE NO. 1; FD&C YELLOW NO. 5

Germ-X 826.000/826AA rev 1
Moisturizing Hand Sanitizer with Aloe

Active ingredient

Ethyl Alcohol 62%

Purpose

Antiseptic

Uses

- to decrease bacteria on the skin that could cause disease
- recommended for repeated use

Warnings

For external use only: hands

Flammable, keep away from fire or flame.

When using this product

- keep out of eyes. In case of contact with eyes, flush thoroughly with water.
- avoid contact with broken skin
- do not inhale or ingest

Stop use and ask a doctor if

- irritation and redness develop
- condition persists for more than 72 hours

Keep out of reach of children.

If swallowed, get medical help or contact a Poison Control Center right away.

Directions

- wet hands thoroughly with product and allow to dry without wiping
- for children under 6, use only under adult supervision
- not recommended for infants

Other information

- do not store above 105⁰F
- may discolor some fabrics
- harmful to wood finishes and plastics

Inactive ingredients

water, carbomer, fragrance, glycerin, isopropyl myristate, Aloe barbadensis leaf juice, tocopheryl acetate, blue 1, yellow 5

Claims

*Effective at eliminating 99.99% of many common harmful germs and bacteria in as little as 15 seconds.

Adverse reaction

Distributed By: UpLift Brands, LLC

St. Louis, MO 63114

1-866 MY GERMX

Principal Display Panel

germ-X®

SINCE 1997

ORIGINAL

MOISTURIZING

HAND SANITIZER

WITH ALOE

Kills 99.99% of Germs*

with vitamin E

8 FL OZ (236 mL)